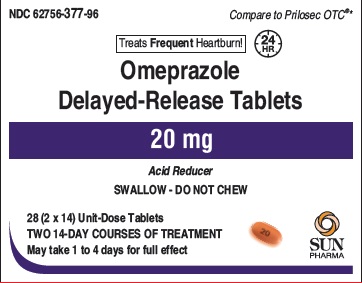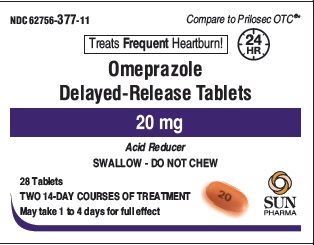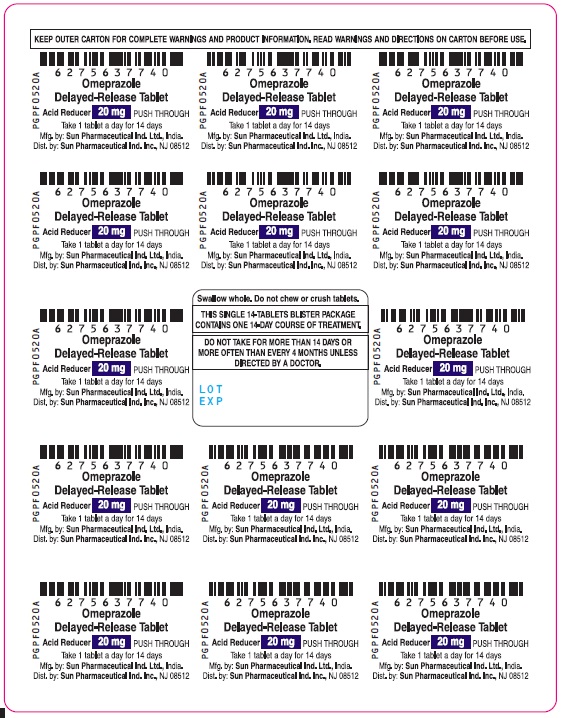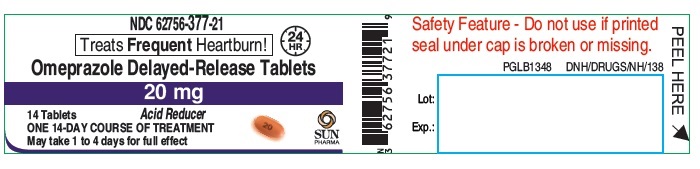 DRUG LABEL: Omeprazole
NDC: 62756-377 | Form: TABLET, DELAYED RELEASE
Manufacturer: Sun Pharmaceutical Industries, Inc.
Category: otc | Type: Human OTC Drug Label
Date: 20250428

ACTIVE INGREDIENTS: OMEPRAZOLE 20 mg/1 1
INACTIVE INGREDIENTS: ANHYDROUS LACTOSE; HYPROMELLOSE, UNSPECIFIED; HYPROMELLOSE ACETATE SUCCINATE 12070923 (3 MM2/S); FERRIC OXIDE RED; FERRIC OXIDE YELLOW; LACTOSE MONOHYDRATE; MONOETHANOLAMINE; METHYLCELLULOSE (1500 MPA.S); PROPYLENE GLYCOL; SODIUM STARCH GLYCOLATE TYPE A POTATO; SODIUM STEARATE; SODIUM STEARYL FUMARATE; SODIUM LAURYL SULFATE; TRIETHYL CITRATE; TALC; TITANIUM DIOXIDE; AMMONIA; FERROSOFERRIC OXIDE; BUTYL ALCOHOL; SHELLAC

Omeprazole Delayed-Release Tablets, 20 mg

Active ingredient(in each tablet)

Omeprazole USP 20 mg

Purpose

Acid reducer

Use

- treats frequent heartburn (occurs 2 or more days a week)
- not intended for immediate relief of heartburn; this drug may take 1 to 4 days for full effect

Warnings

Allergy alert:
do not use if you are allergic to omeprazole
• omeprazole may cause severe skin reactions. Symptoms may include:
• skin reddening • blisters • rash
If an allergic reaction occurs, stop use and seek medical help right away.

Do not use

if you have:

- trouble or pain swallowing food, vomiting with blood, or bloody or black stools
- heartburn with lightheadedness, sweating or dizziness
- chest pain or shoulder pain with shortness of breath; sweating; pain spreading to arms, neck or shoulders; or lightheadedness
- frequent chest pain

These may be signs of a serious condition. See your doctor.

Ask a docotor before use if you have:

- had heartburn over 3 months. This may be a sign of a more serious condition.
- frequent wheezing, particularly with heartburn
- unexplained weight loss
- nausea or vomiting
- stomach pain

Ask a doctor or pharmacist before use if you are

taking a prescription drug. Acid reducers may interact with certain prescription drugs.

Stop use and ask a doctor if

- your heartburn continues or worsens
- you need to take this product for more than 14 days
- you need to take more than 1 course of treatment every 4 months
- you get diarrhea
- you develop a rash or joint pain

If pregnant or breast-feeding,

ask a health professional before use.

Keep out of reach of children.

In case of overdose, get medical help or contact a Poison Control Center right away. (1-800-222-1222)

Directions

- for adults 18 years of age and older
- this product is to be used once a day (every 24 hours), every day for 14 days
- it may take 1 to 4 days for full effect; some people get complete relief of symptoms within 24 hours

14-Day Course of Treatment

- swallow 1 tablet with a glass of water before eating in the morning
- take every day for 14 days
- do not take more than 1 tablet a day
- do not use for more than 14 days unless directed by your doctor
- swallow whole. Do not chew or crush tablets.

Repeated 14-Day Courses (if needed)

- you may repeat a 14-day course every 4 months
- do not take for more than 14 days or more often than every 4 months unless directed by a doctor
- children under 18 years of age: ask a doctor. Heartburn in children may sometimes be caused by a serious condition.

Other information

- read the directions and warnings before use
- keep the carton. It contains important information.
- store at 20 to 25° C (68 to 77° F) and protect from moisture

Inactive ingredients

anhydrous lactose, hypromellose, hypromellose acetate succinate, iron oxide red, iron oxide yellow, lactose monohydrate, methyl cellulose, monoethanolamine, propylene glycol, sodium lauryl sulfate, sodium starch glycolate, sodium stearate, sodium stearyl fumarate, talc, triethyl citrate and titanium dioxide.

The imprinting ink contains ammonium hydroxide, black iron oxide, n-butyl alcohol, propylene glycol and shellac.

Questions or Comments?

Call toll free 1-800-818-4555 weekdays.

Tips of Managing Heartburn

- Do not lie flat or bend over after eating
- Do not wear tight-fitting clothing around the stomach
- Do not eat before bedtime
- Raise the head of your bed
- Avoid heartburn-causing foods such as rich, spicy, fatty or fried foods, chocolate, caffeine, alcohol and certain fruits and vegetables
- Eat slowly and avoid big meals
- If overweight, lose weight
- Quit smoking

Principal Display Panel - Foil

62756-377-40
Omeprazole Delayed-Release Tablet
20 mg
Acid Reducer
PUSH THROUGH

Take 1 tablet a day fo 14 days

Mfg. by: Sun Pharmaceutical Ind Ltd., India.
Dist. by: Sun Pharmaceutical Ind Inc., NJ 08512
PGPF0520A

Principal Display Panel - Blister Carton

NDC 62756-377-96
Compare to Prilosec OTC ® *
Treats Frequent Heartburn! (24 HR)

Compare to Prilosec OTC ® *
Omeprazole Delayed-release Tablets
20 mg
Acid Reducer

SWALLOW - DO NOT CHEW
28 (2 x 14) Unit-Dose Tablets
TWO 14-DAY COURSES OF TREATMENT
May take 1 to 4 days for full effect

Principal Display Panel - Label

NDC 62756-377-21
TreatsFrequentHeartburn!(24 HR)
Omeprazole Delayed-release Tablets
20 mg
Acid Reducer
14 Tablets
ONE 14-DAY COURSE OF TREATMENT
May take 1 to 4 days for full effect

Principal Display Panel - Bottle Carton

NDC 62756-377-11

Compare to Prilosec OTC ® *
Treats Frequent Heartburn! (24 HR)
Omeprazole Delayed-release Tablets
20 mg
Acid Reducer
SWALLOW - DO NOT CHEW
28 Tablets
TWO 14-DAY COURSES OF TREATMENT
May take 1 to 4 days for full effect